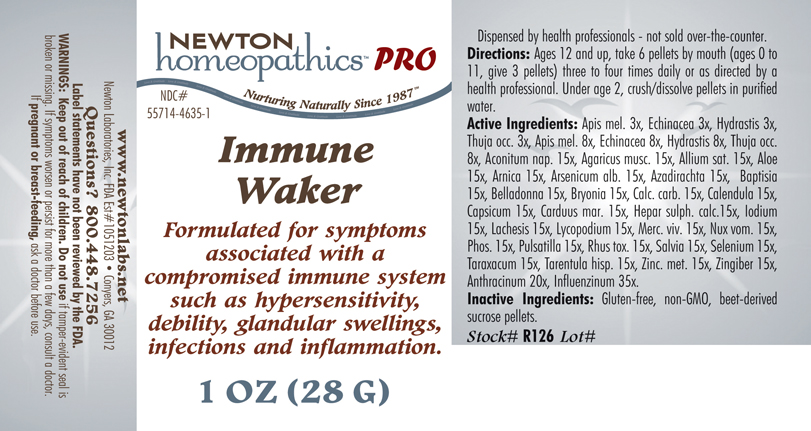 DRUG LABEL: Immune Waker 
NDC: 55714-4635 | Form: PELLET
Manufacturer: Newton Laboratories, Inc.
Category: homeopathic | Type: HUMAN PRESCRIPTION DRUG LABEL
Date: 20141110

ACTIVE INGREDIENTS: Apis Mellifera 8 [hp_X]/1 g; Echinacea, Unspecified 8 [hp_X]/1 g; Goldenseal 8 [hp_X]/1 g; Thuja Occidentalis Leafy Twig 8 [hp_X]/1 g; Aconitum Napellus 15 [hp_X]/1 g; Amanita Muscaria Fruiting Body 15 [hp_X]/1 g; Garlic 15 [hp_X]/1 g; Aloe 15 [hp_X]/1 g; Arnica Montana 15 [hp_X]/1 g; Arsenic Trioxide 15 [hp_X]/1 g; Azadirachta Indica Bark 15 [hp_X]/1 g; Baptisia Tinctoria Root 15 [hp_X]/1 g; Atropa Belladonna 15 [hp_X]/1 g; Bryonia Alba Root 15 [hp_X]/1 g; Oyster Shell Calcium Carbonate, Crude 15 [hp_X]/1 g; Calendula Officinalis Flowering Top 15 [hp_X]/1 g; Capsicum 15 [hp_X]/1 g; Milk Thistle 15 [hp_X]/1 g; Calcium Sulfide 15 [hp_X]/1 g; Iodine 15 [hp_X]/1 g; Lachesis Muta Venom 15 [hp_X]/1 g; Lycopodium Clavatum Spore 15 [hp_X]/1 g; Mercury 15 [hp_X]/1 g; Strychnos Nux-vomica Seed 15 [hp_X]/1 g; Phosphorus 15 [hp_X]/1 g; Pulsatilla Vulgaris 15 [hp_X]/1 g; Toxicodendron Pubescens Leaf 15 [hp_X]/1 g; Sage 15 [hp_X]/1 g; Selenium 15 [hp_X]/1 g; Taraxacum Officinale 15 [hp_X]/1 g; Lycosa Tarantula 15 [hp_X]/1 g; Zinc 15 [hp_X]/1 g; Ginger 15 [hp_X]/1 g; Bacillus Anthracis 20 [hp_X]/1 g; Influenza A Virus 35 [hp_X]/1 g; Influenza B Virus 35 [hp_X]/1 g
INACTIVE INGREDIENTS: Sucrose

Immune Waker

INDICATIONS & USAGE SECTION

Formulated for symptoms associated with a compromised immune system such as hypersensitivity, debility, glandular swellings, infections and inflammation.

DOSAGE & ADMINISTRATION SECTION

Directions: Ages 12 and up, take 6 pellets by mouth (ages 0 to11, give 3 pellets) three to four times daily or as directed by a health professional. Under age 2, crush/dissolve pellets in purified water.

ACTIVE INGREDIENT SECTION

Apis mel. 3x, Echinacea 3x, Hydrastis 3x, Thuja occ. 3x, Apis mel. 8x, Echinacea 8x, Hydrastis 8x, Thuja occ. 8x, Aconitum nap. 15x, Agaricus musc. 15x, Allium sat. 15x, Aloe 15x, Arnica 15x, Arsenicum alb. 15x, Azadirachta 15x, Baptisia 15x, Belladonna 15x, Bryonia 15x, Calc. carb. 15x, Calendula 15x, Capsicum 15x, Carduus mar. 15x, Hepar sulph. calc. 15x, Iodium 15x, Lachesis 15x, Lycopodium 15x, Merc. viv. 15x, Nux vom. 15x, Phos. 15x, Pulsatilla 15x, Rhus tox. 15x,. Salvia 15x, Selenium 15x, Taraxacum 15x, Tarentula hisp. 15x, Zinc. met. 15x, Zingiber 15x, Anthracinum 20x, Influenzinum 35x.

PURPOSE SECTION

Formulated for symptoms associated with a compromised immune system such as hypersensitivity, debility, glandular swellings, infections and inflammation.

INACTIVE INGREDIENT SECTION

Inactive Ingredients: Gluten-free, non-GMO, beet-derived sucrose pellets.

QUESTIONS SECTION

www.newtonlabs.net Newton Laboratories, Inc. FDA Est # 1051203 - Conyers, GA 30012 Questions? 1.800.448.7256

WARNINGS SECTION

Warning: Keep out of reach of children. Do not use if tamper-evident seal is broken or missing. If symptoms worsen or persist for more than a few days, consult a doctor. If pregnant or breast-feeding, ask a doctor before use.

PREGNANCY OR BREAST FEEDING SECTION

If pregnant or breast-feeding, ask a doctor before use.

KEEP OUT OF REACH OF CHILDREN SECTION

Keep out of reach of children.